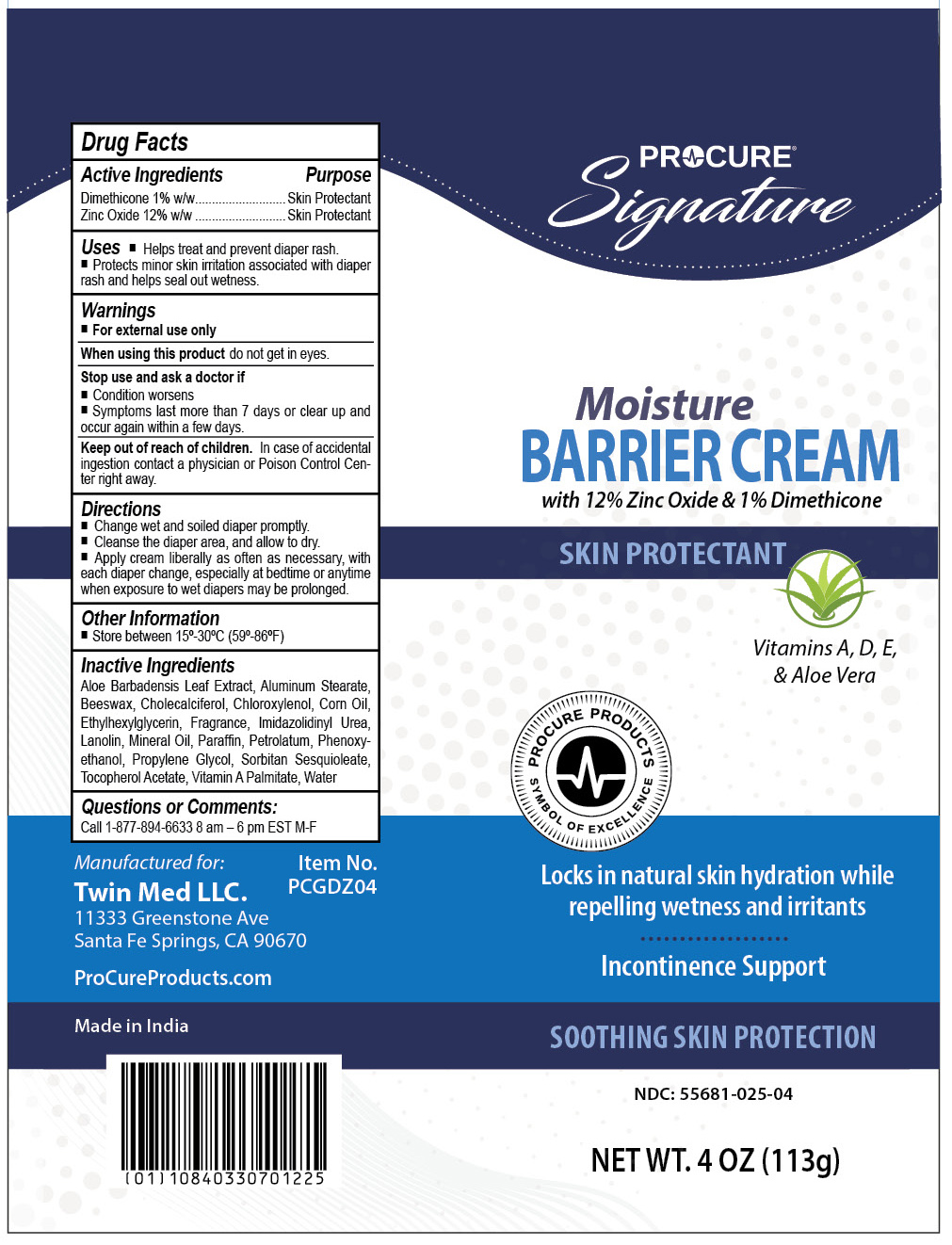 DRUG LABEL: ProCure Moisture Barrier
NDC: 55681-025 | Form: CREAM
Manufacturer: Twin Med LLC
Category: otc | Type: HUMAN OTC DRUG LABEL
Date: 20250714

ACTIVE INGREDIENTS: ZINC OXIDE 12 g/100 g; DIMETHICONE 1 g/100 g
INACTIVE INGREDIENTS: CORN OIL; IMIDAZOLIDINYL UREA; LANOLIN; MINERAL OIL; WATER; PARAFFIN; ALOE VERA LEAF; CHOLECALCIFEROL; PHENOXYETHANOL; .ALPHA.-TOCOPHEROL ACETATE; SORBITAN SESQUIOLEATE; VITAMIN A PALMITATE; PETROLATUM; CHLOROXYLENOL; PROPYLENE GLYCOL; ETHYLHEXYLGLYCERIN; ALUMINUM STEARATE; BEESWAX

Active Ingredients

Dimethicone 1% w/w

Zinc Oxide 12% w/w

Purpose

Skin Protectant

Uses

- Helps treat and prevent diaper rash.
- Protects minor skin irritation associated with diaper rash and helps seal out wetness.

Warnings

- For external use only

When using this product do not get into the eyes

Stop use and ask a doctor if

- Condition worsens
- Symptoms last more than 7 days or clear up and occur again within a few days

Keep out of reach of children. In case of accidental ingestion contact a physician or Poison Control Center right away.

Directions

- Change wet and soiled diaper promptly
- Cleanse the diaper area, and allow to dry
- Apply cream liberally as often as necessary, with each diaper change, especially at bedtime or anytime when exposure to wet diapers may be prolonged

Inactive Ingredients

Aloe Barbadensis Leaf Extract, Aluminum Stearate, Beeswax, Cholecalciferol, Chloroxylenol, Corn Oil, Ethylhexylglycerin, Fragrance, Imidazolidinyl Urea, Lanolin, Mineral Oil, Paraffin, Petrolatum, Phenoxyethanol, Propylene Glycol, Sorbitan Sesquioleate, Tocopherol Acetate, Vitamin A Palmitate, Water